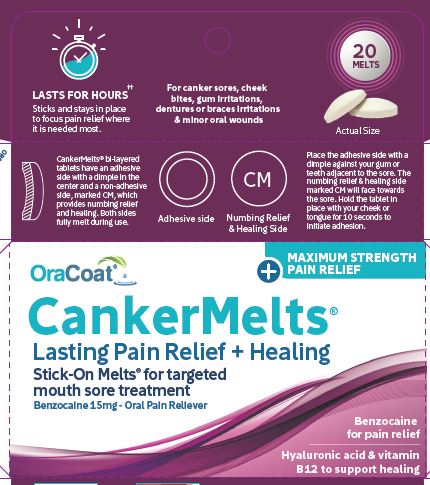 DRUG LABEL: CankerMelts
NDC: 68229-700 | Form: LOZENGE
Manufacturer: Quest Products, LLC
Category: otc | Type: HUMAN OTC DRUG LABEL
Date: 20251204

ACTIVE INGREDIENTS: BENZOCAINE 15 mg/1 1
INACTIVE INGREDIENTS: HYDROXYPROPYLCELLULOSE; HYALURONIC ACID; PEPPERMINT OIL; SODIUM BICARBONATE; MAGNESIUM STEARATE; XYLITOL; METHYLCOBALAMIN; MALTODEXTRIN; CARBOXYMETHYLCELLULOSE SODIUM, UNSPECIFIED FORM; ACACIA

CankerMelts®

Active Ingredient (in each self-adhering tablet)

Benzocaine 15mg

Purpose

Oral Pain Relief

Uses

for temporary relief of pain associated with:

- canker sores
- minor irritation
- mouth sores

Warnings

Methemoglobinemea warning:

Use of this product may cause methemoglobinemea, a serious- condition that must be treated promptly because it reduces the amount of oxygen carried in blood. This can occur even if you have used this product before. Stop use and seek immediate medical attention if you or a child in your care develops:

- pale, gray, or blue colored skin (cyanosis)
- headache
- rapid heart rate
- shortness of breath
- dizziness or lightheadedness
- fatigue or lack of energy

Allergy alert:

Do not use this product if you have a history of allergy to local anesthetics such as procaine, butacaine, benzocaine, or other "caine" anesthetics.

Do not use:

- this product for more than 7 days unless directed by a doctor or dentist
- in children under 5 years of age

When using this product

do not exceed recommended dosage.

Stop use and ask a doctor or dentist if:

- if sore mouth symptoms do not improve in 7 days
- if irritation, pain, or redness persists or worsens
- if swelling, rash or fever develops

If pregnant or breast-feeding,

ask a health professional before use.

Keep out of reach of children

in case of overdose, get medical help or contact a Poison Control Center right away.

Directions

Adults and children age 5 and older:

Affix one tablet as directed below and allow to slowly dissolve in the mouth. May be repeated every 2 hours as needed or directed by a doctor or dentist. This product may last over 2 hours.

Placement:

CankerMelts are bi-layered tablets with a dimple on the adhesive side and a pain reliever on the domed side marked CM. Place the adhesive side with a dimple against teeth or gums or braces or appliance. Place opposite or adjacent to the sore. Hold tablet in place with your cheek or tongue for 10 seconds to initiate adhesion. Adhesion will strengthen over the next few minutes. It may be removed at any time.

Children under 5 years of age:

Do not use.

Other Information

- Protect from humidity
- Store at 15°C - 30°C (59°F - 86°F)

Inactive Ingredients

Acacia gum, cellulose gum, hyaluronic acid, magnesium stearate, maize dextrin, methylcobalamin (vitamin B12), mint oil, sodium bicarbonate, xylitol